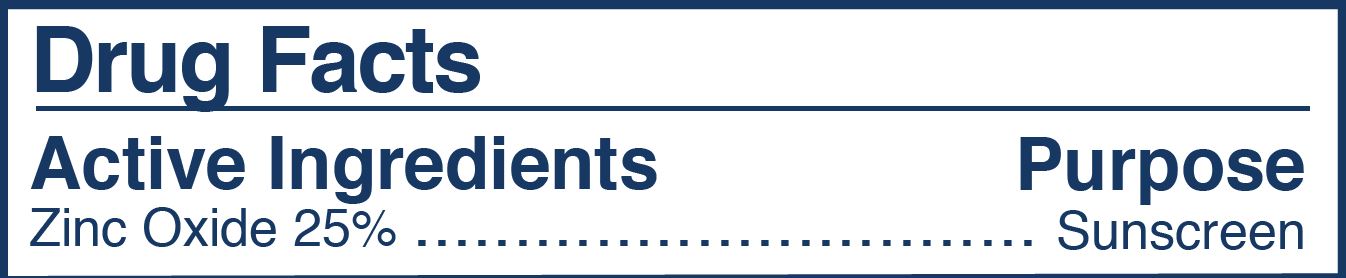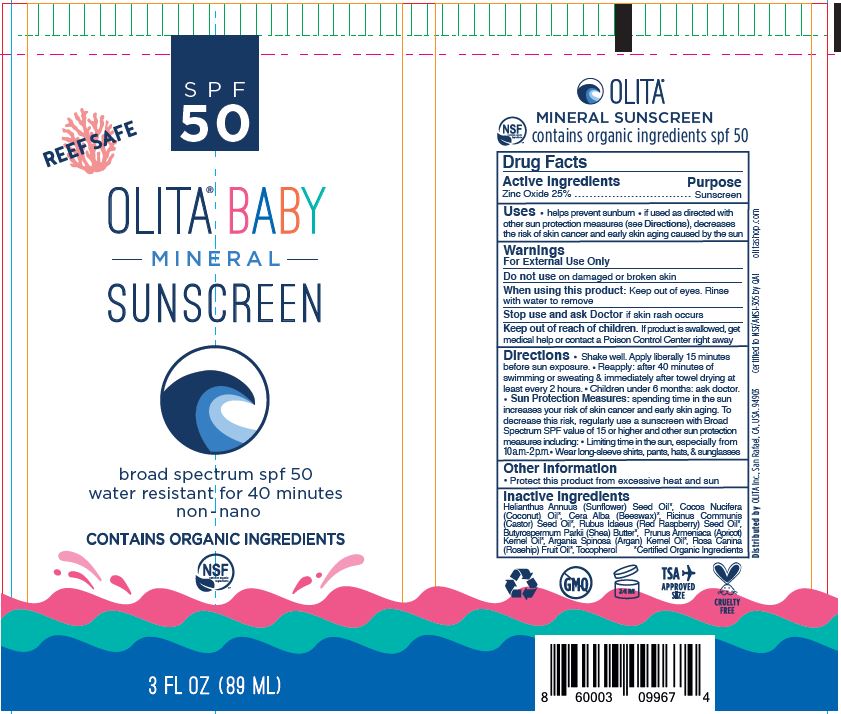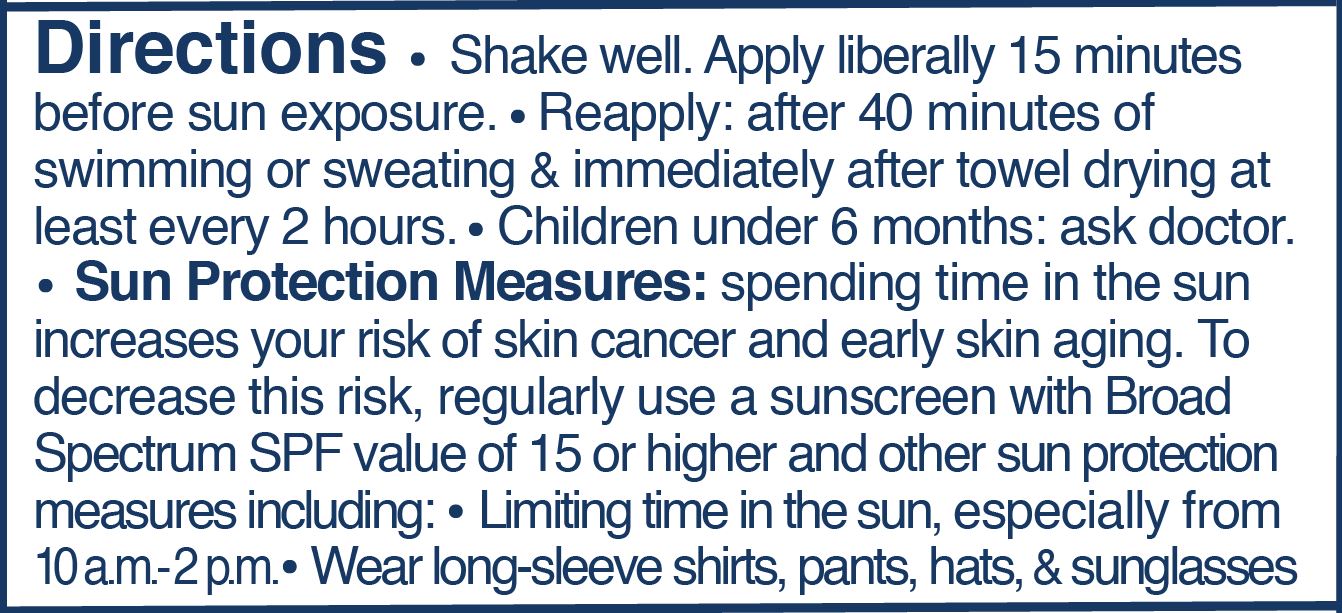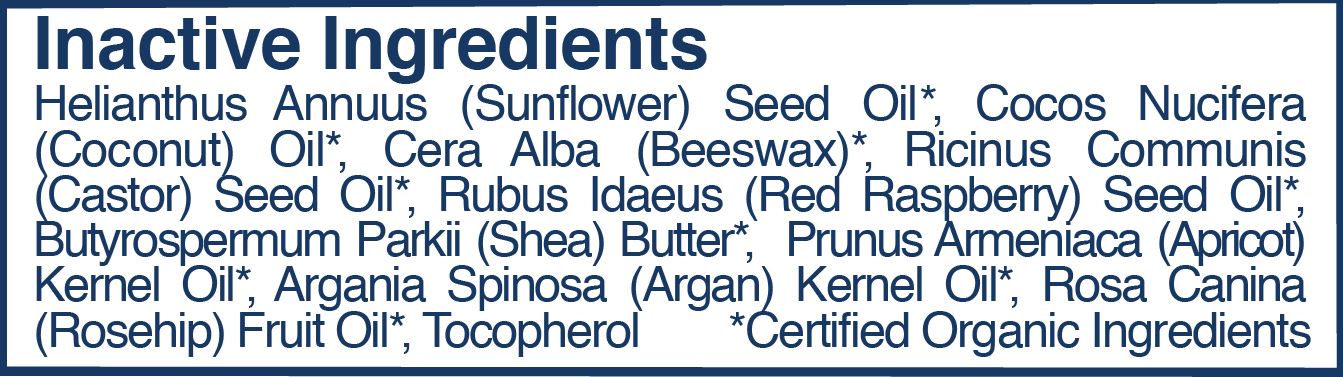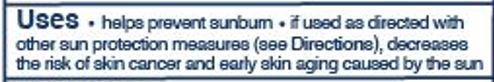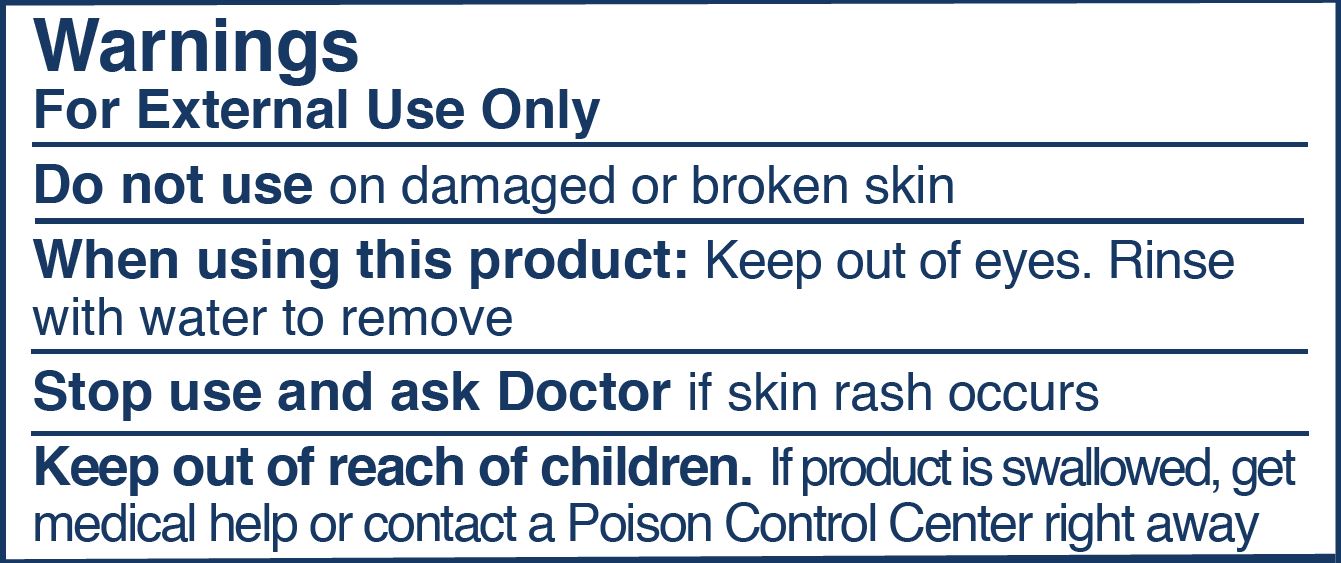 DRUG LABEL: Baby Mineral Sunscreen, SPF 30
NDC: 62932-259 | Form: OINTMENT
Manufacturer: Private Label Select Ltd CO
Category: otc | Type: HUMAN OTC DRUG LABEL
Date: 20210101

ACTIVE INGREDIENTS: ZINC OXIDE 25 g/100 g
INACTIVE INGREDIENTS: WHITE WAX; .ALPHA.-TOCOPHEROL, D-; .BETA.-TOCOPHEROL; .DELTA.-TOCOPHEROL; SUNFLOWER OIL; COCONUT OIL; RASPBERRY SEED OIL; .GAMMA.-TOCOPHEROL; CASTOR OIL; ROSA CANINA SEED OIL; SHEA BUTTER; APRICOT KERNEL OIL

Olita Inc., Baby Mineral Sunscreen, SPF 30